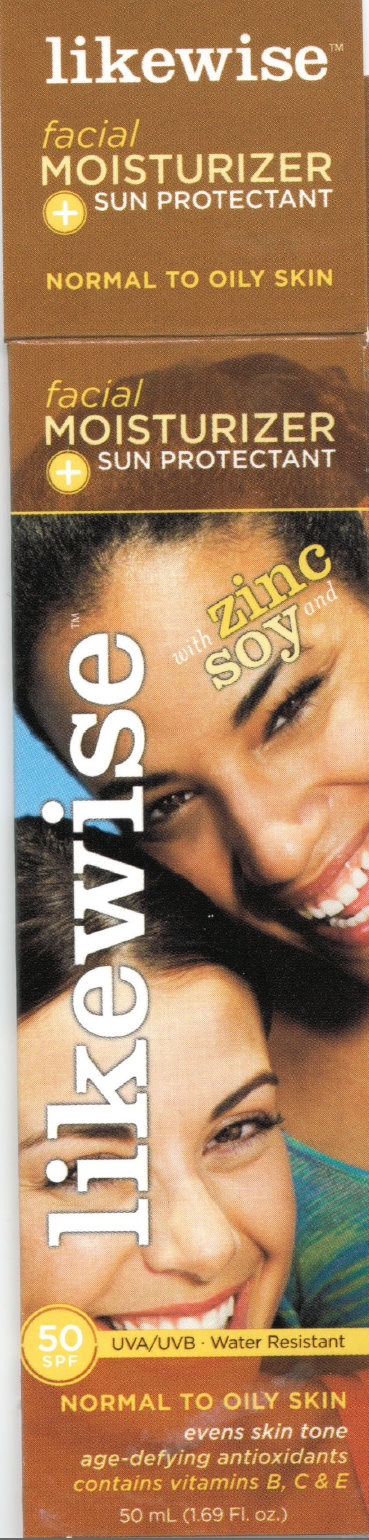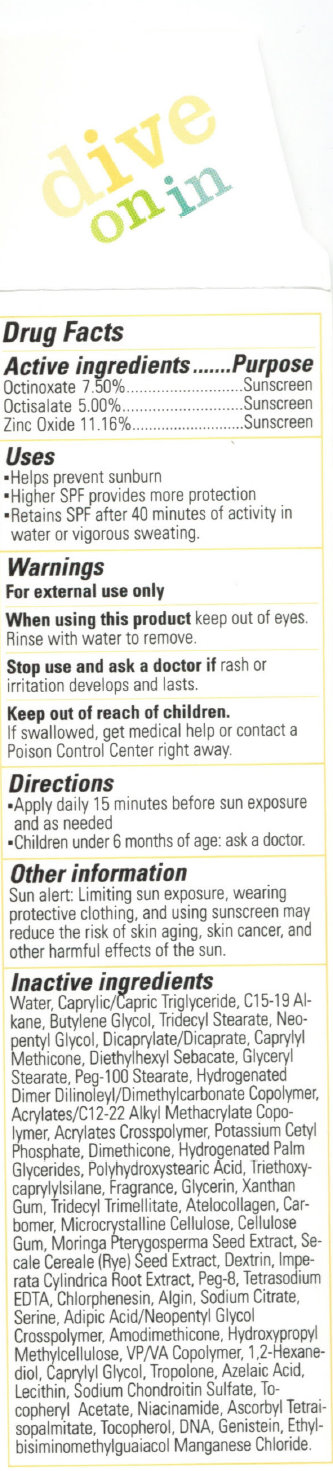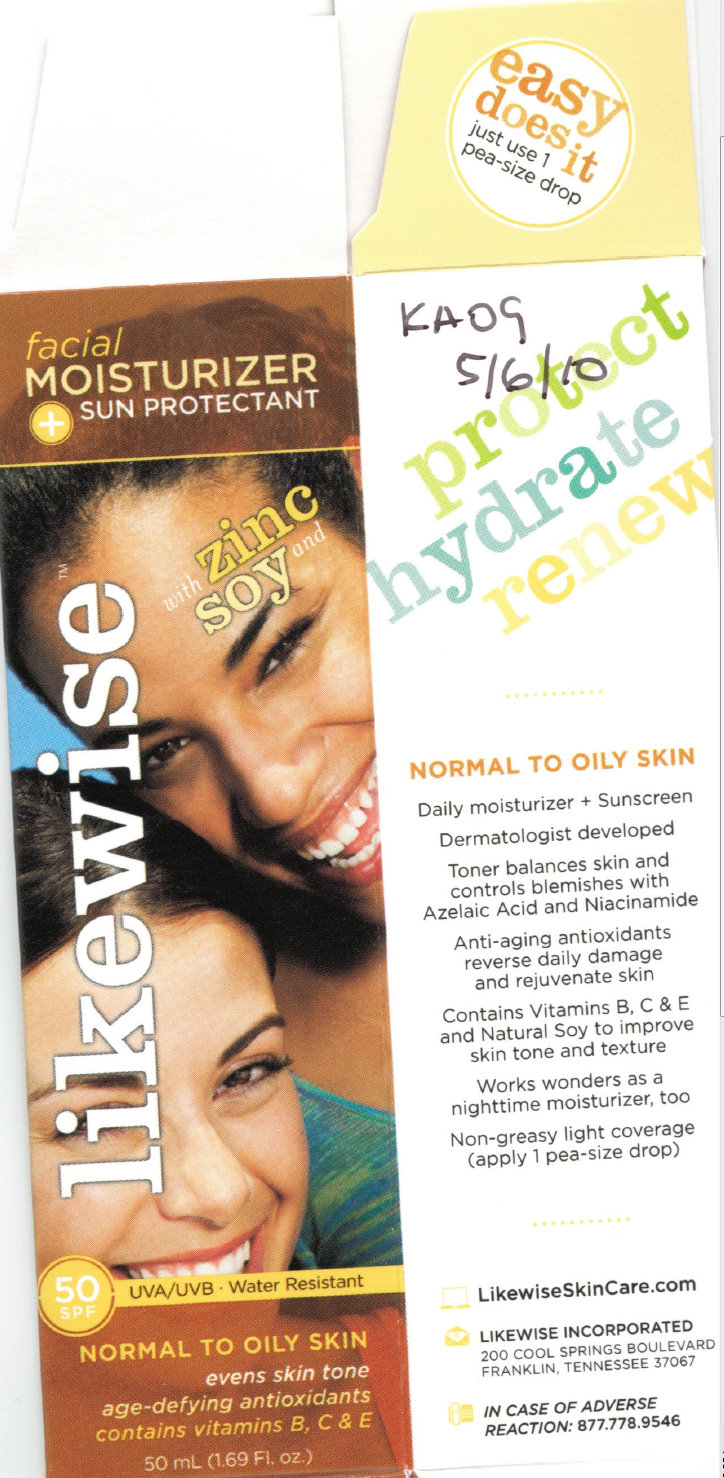 DRUG LABEL: Likewise Facial Moisturizer - Sun Protectant SPF 50 Normal to Oily Skin
NDC: 76229-345 | Form: CREAM
Manufacturer: Likewise Incorporated
Category: otc | Type: HUMAN OTC DRUG LABEL
Date: 20231212

ACTIVE INGREDIENTS: OCTINOXATE 75 mg/1 mL; OCTISALATE 50 mg/1 mL; ZINC OXIDE 111.6 mg/1 mL
INACTIVE INGREDIENTS: WATER; MEDIUM-CHAIN TRIGLYCERIDES; BUTYLENE GLYCOL; TRIDECYL STEARATE; NEOPENTYL GLYCOL; GLYCERYL MONOSTEARATE; PEG-100 STEARATE; DIMETHICONE; HYDROGENATED PALM GLYCERIDES; TRIETHOXYCAPRYLYLSILANE; GLYCERIN; XANTHAN GUM; TRIDECYL TRIMELLITATE; CELLULOSE, MICROCRYSTALLINE; CARBOXYMETHYLCELLULOSE SODIUM; MORINGA OLEIFERA SEED; RYE; ICODEXTRIN; IMPERATA CYLINDRICA ROOT; POLYETHYLENE GLYCOL 400; EDETATE SODIUM; CHLORPHENESIN; SODIUM ALGINATE; SODIUM CITRATE; SERINE; ADIPIC ACID; 1,2-HEXANEDIOL; CAPRYLYL GLYCOL; TROPOLONE; AZELAIC ACID; SODIUM CHONDROITIN SULFATE (PORCINE; 5500 MW); NIACINAMIDE; TOCOPHEROL; HERRING SPERM DNA; GENISTEIN

Likewise Moisturizer - Sun Protectant SPF 50 Normal to Oily Skin

ACTIVE INGREDIENT

Active Ingredients..............Purpose Octinoxate 7.50%............Sunscreen Octisalate 5.00%.............Sunscreen Zinc Oxide 11.16%..........Sunscreen

PURPOSE

Uses - Helps prevent sunburn - Higher SPF provides more protection - Retains SPF after 40 minutes of activity in water or vigorous sweating.

Uses

- Helps prevent sunburn
- Higher SPF provides more protection
- Retains SPF after 40 minutes of activity in water or vigorous sweating.

Warnings For external use only

When using this product keep out of eyes. Rinse with water to remove.

Stop use and ask a doctor if rash or irritation develops and lasts.

Keep out of reach of children.

If swallowed, get medical help or contact a Poison Control Center right away.

OTHER SAFETY INFORMATION

If swallowed, get medical help or contact a Poison Control Center right away.

DOSAGE AND ADMINISTRATION

Directions - Apply daily 15 minutes before sun exposure and as needed - Children under 6 months of age: ask a doctor.

Other information Sun alert: Limiting sun exposure, wearing protective clothing, and using sunscreen may reduce the risk of skin aging, skin cancer, and other harmful effects of the sun.

INACTIVE INGREDIENT

Inactive ingredients Water, Caprylic/Capric Triglyceride, C15-19 Alkane, Butylene Glycol, Tridecyl Stearate, Neopentyl Glycol, Dicaprylate/Dicaprate, Caprylyl Methicone, Diethylhexyl Sebacate, Glyceryl Stearate, Peg-100 Stearate, Hydrogenated Dimer Dilinoleyl/Dimethylcarbonate Copolymer, Acrylates/C12-22 Alkyl Methacrylate Copolymer, Acrylates Crosspolymer, Potassium CetylPhosphate, Dimethicone, Hydrogenated Palm Glycerides, Polyhydroxystearic Acid, Triethoxycaprylylsilane, Fragrance, Glycerin, Xanthan Gum, Tridecyl Trimellitate, Atelocollagen, Carbomer, Microcrystalline Cellulose, Cellulose Gum, Moringa Pterygosperma Seed Extract, Secale Cereale (Rye) Seed Extract, Dextrin, Imperata Cylindrica Root Extract, Peg-8, Tetrasodium EDTA, Chlorphenesin, Algin, Sodium Citrate, Serine, Adipic Acid/Neopentyl Glycol Crosspolymer, Amodimethicone, Hydroxypropyl Methylcellulose, VP/VA Copolymer, 1,2-Hexanediol, Caprylyl Glycol, Tropolone, Azelaic Acid, Lecithin, Sodium Chondroitin Sulfate, Tocopheryl Acetate, Niacinamide, Ascorbyl Tetraisopalmitate, Tocopherol, DNA, Genistein, Ethylbisiminomethylguaiacol Manganese Chloride.

DESCRIPTION

protect hydrate renew . . . . . . . NORMAL TO OILY SKIN Daily moisturizer + Sunscreen Dermatologist developed Toner balances skin and controls blemishes with Azelaic Acid and Niacimide Anti-aging antioxidants reverse daily damage and rejuvenate skin Contains Vitamins B, C and E and Natural Soy to improve skin tone and texture Works wonders as a nighttime moisturizer, too Non-greasy light coverage (apply 1 pea-size drop). . . . . . LikewiseSkinCare.com LIKEWISE INCORPORATED 200 COOL SPRINGS BOULEVARD FRANKLIN, TENNESSEE 37067 IN CASE OF ADVERSE REACTION: 877.778.9546

PACKAGE LABEL

likewise facial MOISTURIZER + SUN PROTECTANT NORMAL TO OILY SKIN facial MOISTURIZER + SUN PROTECTANT likewise with Zinc Soy and 50 SPF UVA/UVB - Water Resistant NORMAL TO OILY SKIN evens skin tone age-defying antioxidants contains vitamins B, C and E 50 mL (1.69 Fl.oz.)

PACKAGE LABEL

dive on in Drug Facts

PACKAGE LABEL

facial MOISTURIZER + SUN PROTECTANT likewise with Zinc Soy and 50 SPF UVA/UVB - Water Resistant NORMAL TO OILY SKIN evens skin tone age-defying antioxidants contains vitamins B, C and E 50 mL (1.69 Fl.oz.) easy does it just use 1 pea-size drop protect hydrate renew